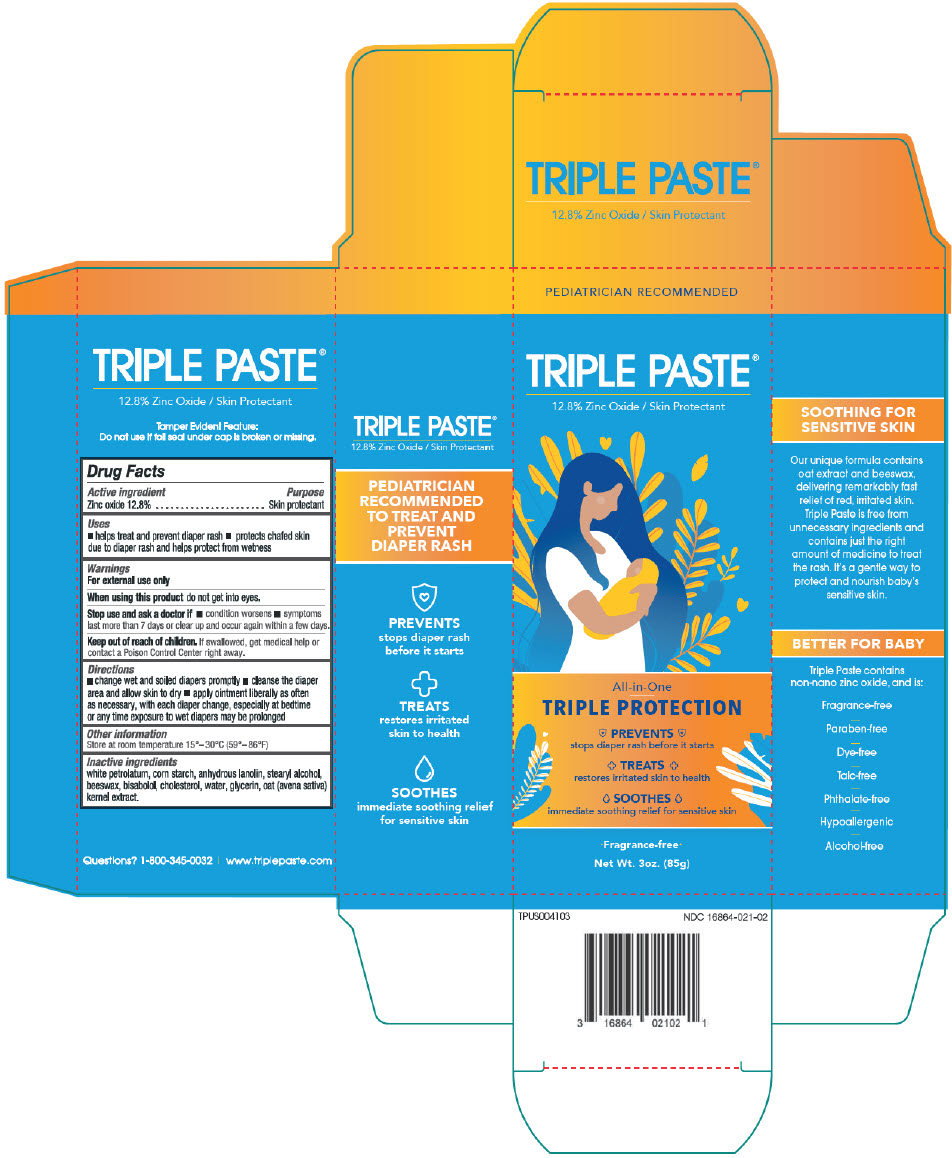 DRUG LABEL: Triple Diaper Rash
NDC: 16864-021 | Form: OINTMENT
Manufacturer: Advantice Health, LLC
Category: otc | Type: HUMAN OTC DRUG LABEL
Date: 20241009

ACTIVE INGREDIENTS: ZINC OXIDE 12.8 g/100 g
INACTIVE INGREDIENTS: WHITE PETROLATUM; STARCH, CORN; LANOLIN; STEARYL ALCOHOL; YELLOW WAX; LEVOMENOL; CHOLESTEROL; WATER; GLYCERIN; OAT

Triple Paste®Diaper Rash Ointment

Drug Facts

Active ingredient

Zinc oxide 12.8%

Purpose

Skin protectant

Uses

- helps treat and prevent diaper rash
- protects chafed skin due to diaper rash and helps protect from wetness

Warnings

For external use only

When using this productdo not get into eyes.

Stop use and ask a doctor if

- condition worsens
- symptoms last more than 7 days or clear up and occur again within a few days.

Keep out of reach of children.If swallowed, get medical help or contact a Poison Control Center right away.

Directions

- change wet and soiled diapers promptly
- cleanse the diaper area and allow skin to dry
- apply ointment liberally as often as necessary, with each diaper change, especially at bedtime or any lime exposure to wet diapers may be prolonged

Other information

Store at room temperature 15°-30°C (59°-86°F)

Inactive ingredients

white petrolatum, com starch, anhydrous lanolin, stearyl alcohol, beeswax, bisabolol, cholesterol, water, glycerin, oat (avena saliva) kernel extract.

Questions?

1-800-345-0032

Distributed by Advantice Health, LLC
Cedar Knolls, NJ 07927

PRINCIPAL DISPLAY PANEL - 85 g Tube Carton

PEDIATRICIAN RECOMMENDED

TRIPLE PASTE®
12.8% Zinc Oxide / Skin Protectant

All-in-One

TRIPLE PROTECTION

PREVENTS
stops diaper rash before it starts

TREATS
restores irritated skin to health

SOOTHES
immediate soothing relief for sensitive skin

•Fragrance-free•

Net Wt. 3oz. (85g)